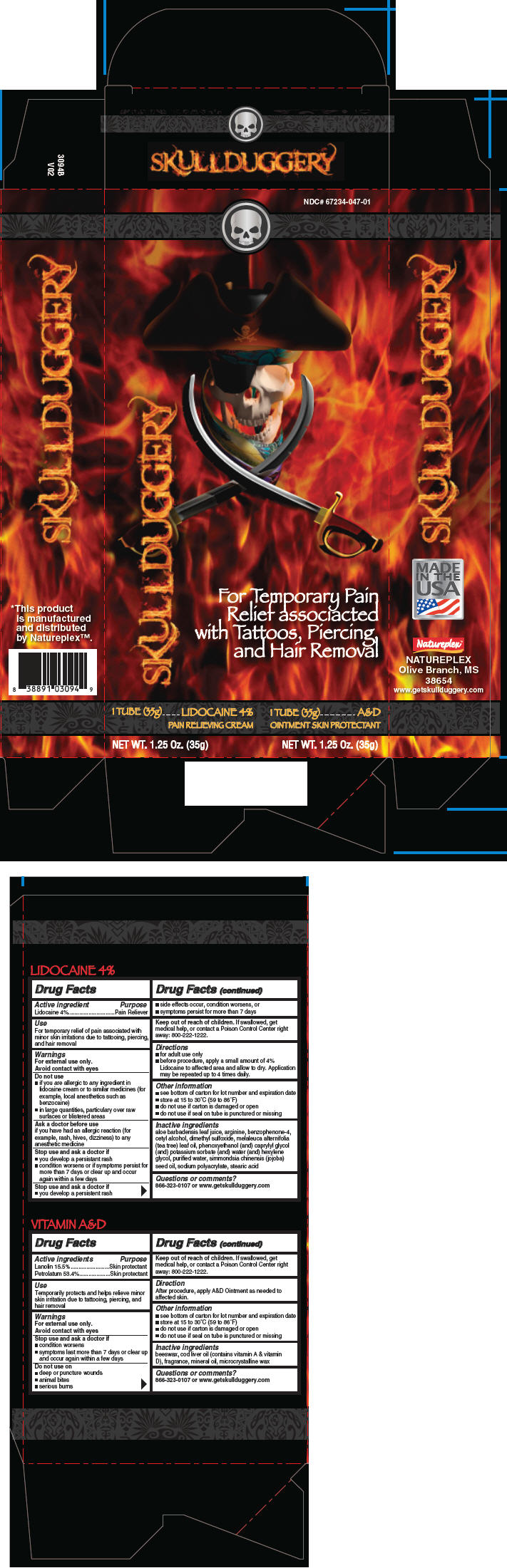 DRUG LABEL: Skullduggery Pain Relief and Skin Protection for Tattoos
NDC: 67234-047 | Form: KIT | Route: TOPICAL
Manufacturer: Natureplex, LLC
Category: otc | Type: HUMAN OTC DRUG LABEL
Date: 20170410

ACTIVE INGREDIENTS: Lanolin 155 mg/1 g; Petrolatum 534 mg/1 g; Lidocaine 40 mg/1 g
INACTIVE INGREDIENTS: YELLOW WAX; COD LIVER OIL; LIGHT MINERAL OIL; MICROCRYSTALLINE WAX; ALOE VERA LEAF; SULISOBENZONE; CETYL ALCOHOL; DIMETHYL SULFOXIDE; CAPRYLYL GLYCOL; ARGININE; WATER; JOJOBA OIL; SODIUM POLYACRYLATE (2500000 MW); STEARIC ACID; TEA TREE OIL

Skullduggery Pain Relief and Skin Protection for Tattoos

LIDOCAINE 4%

Drug Facts

Active ingredient

Lidocaine 4%

Purpose

Pain Reliever

Use

For temporary relief of pain associated with minor skin irritations due to tattooing, piercing, and hair removal

Warnings

For external use only.

Avoid contact with eyes

Do not use

- if you are allergic to any ingredient in lidocaine cream or to similar medicines (for example, local anesthetics such as benzocaine)
- in large quantities, particulary over raw surfaces or blistered areas

Ask a doctor before use if you have had an allergic reaction (for example, rash, hives, dizziness) to any anesthetic medicine

Stop use and ask a doctor if

- you develop a persistant rash
- condition worsens or if symptoms persist for more than 7 days or clear up and occur again within a few days

Stop use and ask a doctor if

- you develop a persistent rash
- side effects occur, condition worsens, or
- symptoms persist for more than 7 days

Keep out of reach of children. If swallowed, get medical help, or contact a Poison Control Center right away: 800-222-1222.

Directions

- for adult use only
- before procedure, apply a small amount of 4% Lidocaine to affected area and allow to dry. Application may be repeated up to 4 times daily.

Other information

- see bottom of carton for lot number and expiration date
- store at 15 to 30°C (59 to 86°F)
- do not use if carton is damaged or open
- do not use if seal on tube is punctured or missing

Inactive ingredients

aloe barbadensis leaf juice, arginine, benzophenone-4, cetyl alcohol, dimethyl sulfoxide, melaleuca alternifolia (tea tree) leaf oil, phenoxyethanol (and) caprylyl glycol (and) potassium sorbate (and) water (and) hexylene glycol, purified water, simmondsia chinensis (jojoba) seed oil, sodium polyacrylate, stearic acid

Questions or comments?

866-323-0107 or www.getskullduggery.com

VITAMIN A&D

Drug Facts

ACTIVE INGREDIENT

Active ingredients | Purpose
Lanolin 15.5% | Skin protectant
Petrolatum 53.4% | Skin protectant

Use

Temporarily protects and helps relieve minor skin irritation due to tattooing, piercing, and hair removal

Warnings

For external use only.

Avoid contact with eyes

Stop use and ask a doctor if

- condition worsens
- symptoms last more than 7 days or clear up and occur again within a few days

Do not use on

- deep or puncture wounds
- animal bites
- serious burns

Keep out of reach of children. If swallowed, get medical help, or contact a Poison Control Center right away: 800-222-1222.

Direction

After procedure, apply A&D Ointment as needed to affected skin.

Other information

- see bottom of carton for lot number and expiration date
- store at 15 to 30°C (59 to 86°F)
- do not use if carton is damaged or open
- do not use if seal on tube is punctured or missing

Inactive ingredients

beeswax, cod liver oil (contains vitamin A & vitamin D), fragrance, mineral oil, microcrystalline wax

Questions or comments?

866-323-0107 or www.getskullduggery.com

This product
is manufactured
and distributed
by Natureplex™.

PRINCIPAL DISPLAY PANEL - Kit Carton

SKULLDUGGERY

NDC# 67234-047-01

For Temporary Pain
Relief associated
with Tattoos, Piercing,
and Hair Removal

1 TUBE (35g)
LIDOCAINE 4%
PAIN RELIEVING CREAM

NET WT. 1.25 Oz. (35g)

1 TUBE (35g)
A&D
OINTMENT SKIN PROTECTANT

NET WT. 1.25 Oz. (35g)